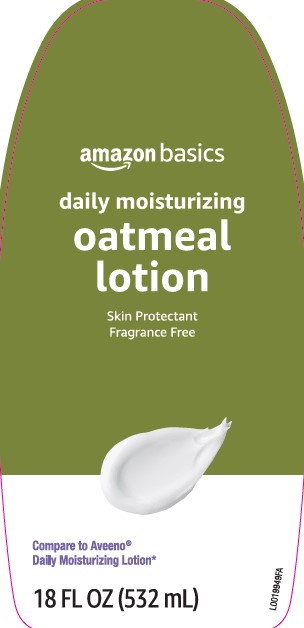 DRUG LABEL: Daily Moisturizing
NDC: 72288-619 | Form: LOTION
Manufacturer: Amazon.com Services LLC
Category: otc | Type: HUMAN OTC DRUG LABEL
Date: 20250217

ACTIVE INGREDIENTS: DIMETHICONE 13 mg/1 g
INACTIVE INGREDIENTS: WATER; GLYCERIN; DISTEARYLDIMONIUM CHLORIDE; PETROLATUM; ISOPROPYL PALMITATE; CETYL ALCOHOL; OAT KERNEL OIL; BENZYL ALCOHOL; SODIUM CHLORIDE

Basics 619.003-619AC rev 2
Daily Moisturizing Lotion

Claim

The basic idea: highly rated products at low prices.

Active ingredient

Dimethicone 1.3%

Purpose

Skin protectant

Use

- helps prevent and temporarily protects chafed, chapped, or cracked skin
- helps protect from the drying effects of wind and cold weather

Warnings

For external use only

When using this product

- do not get into eyes

Stop use and ask a doctor if

- condition worsens
- symptoms last more than 7 days or clear up and occur again within a few days

Do not use on

- deep or puncture wounds
- animal bites
- serious burns

Keep out of reach of children.

If swallowed, get medical help or contact a Poison Control Center right away.

Directions

apply as needed

Inactive ingredients

water, glycerin, distearyldimonium chloride, petrolatum, isopropyl palmitate, cetyl alcohol, Avena sativa (oat) kernel flour, benzyl alcohol, sodium chloride

ADVERSE REACTIONS SECTION

*This product is not manufactured or distributed by Johnson & Johnson Consumer Products Company, distributor of Aveeno Daily Moisturizing Lotion

DISTRIBUTED BY:

Amazon.com Services LLC

Seattle, WA 98109

1-877-485-0385

amazon

© 2021 Amazon.com, Inc., or its affiliates.

All rights reserved.

www.amazon.com/amazonbasics

"Alexa, reorder Amazon Basics Lotion."

principal display panel

amazon basics

daily moisturizing

oatmeal

lotion

Skin Protectant

Fragrance Free

Compare to Aveeno Daily Moisturizing Lotion

18 FL OZ (532 mL)